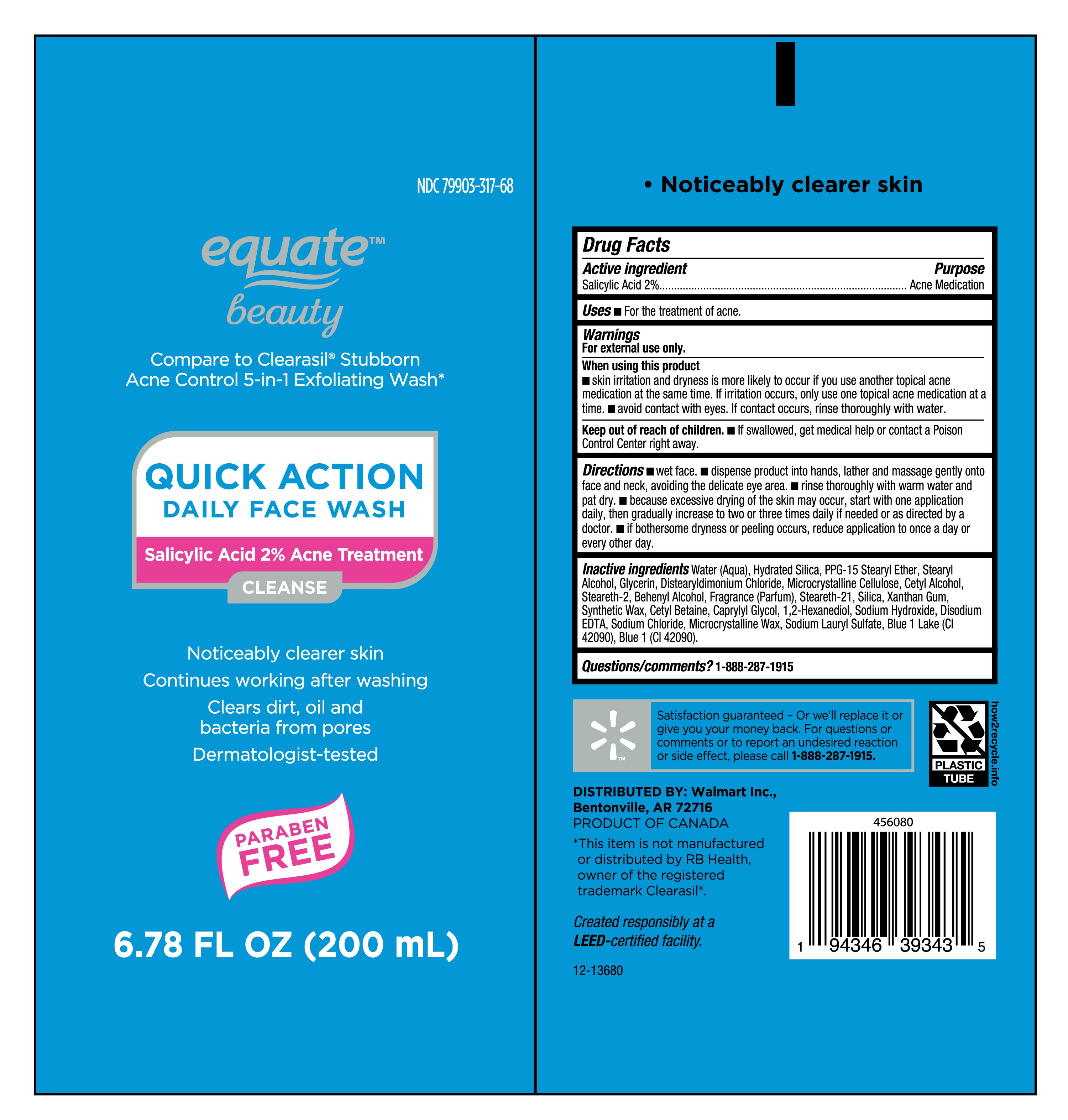 DRUG LABEL: Equate
NDC: 79903-317 | Form: CREAM
Manufacturer: Walmart INC
Category: otc | Type: HUMAN OTC DRUG LABEL
Date: 20250414

ACTIVE INGREDIENTS: SALICYLIC ACID 20 mg/1 mL
INACTIVE INGREDIENTS: MICROCRYSTALLINE CELLULOSE; XANTHAN GUM; WATER; SYNTHETIC WAX (540 MW); HYDRATED SILICA; STEARETH-2; FRAGRANCE CLEAN ORC0600327; CAPRYLYL GLYCOL; STEARETH-21; CETYL ALCOHOL; BEHENYL ALCOHOL; SODIUM CHLORIDE; CETYL BETAINE; SODIUM HYDROXIDE; STEARYL ALCOHOL; BLUE 1 LAKE; SILICA; GLYCERIN; SODIUM LAURYL SULFATE; BLUE 1; DISTEARYLDIMONIUM CHLORIDE; MICROCRYSTALLINE WAX; 1,2-HEXANEDIOL; EDETATE DISODIUM; PPG-15 STEARYL ETHER

NDC- 79903-317, Acne Control 5 in 1 Exfoliating Wash.

Active Ingredient

Salicylic Acid 2%

Purpose

Acne Medication

Uses

- For the treatment of acne.

Warnings

For External use only.

When using this product

- Skin irritation and dryness is more likely to occur if you use another topical acne medication at the same time.If irritation occurs, use only one topical acne medication at a time.
- Avoid contact with eyes. If contact occurs, rinse thoroughly with water.

Keep out of reach of children.

- If swallowed, get medical help or contact a Poison Control Center right away.

Directions

- Wet face.
- dispense product into hands, lather and massage gently onto face and neck, avoiding the delicate eye area.
- Rinse thoroughly with warm water and pat dry.
- because excessive drying of the skin may occur, start with one application daily, then gradually increase to two or three times daily if needed or as directed by a doctor.
- if bothersome dryness or peeling occurs, reduce application to once a day or every other day.

Inactive Ingredients

Water (Aqua), Hydrated Silica, PPG-15 Stearyl Ether, Stearyl Alcohol, Glycerin, Distearyldimonium Chloride, Microcrystalline Cellulose, Cetyl Alcohol, Steareth-2, Behenyl Alcohol, Fragrance (Parfum), Steareth-21, Silica, Xanthan Gum, Synthetic Wax, Cetyl Betaine, Caprylyl Glycol, 1,2-Hexanediol, Sodium Hydroxide, Disodium EDTA, Sodium Chloride, Microcrystalline Wax, Sodium Lauryl Sulfate, Blue 1 Lake (CI 42090), Blue 1 (CI 42090).

Questions/comments?

1-888-287-1915